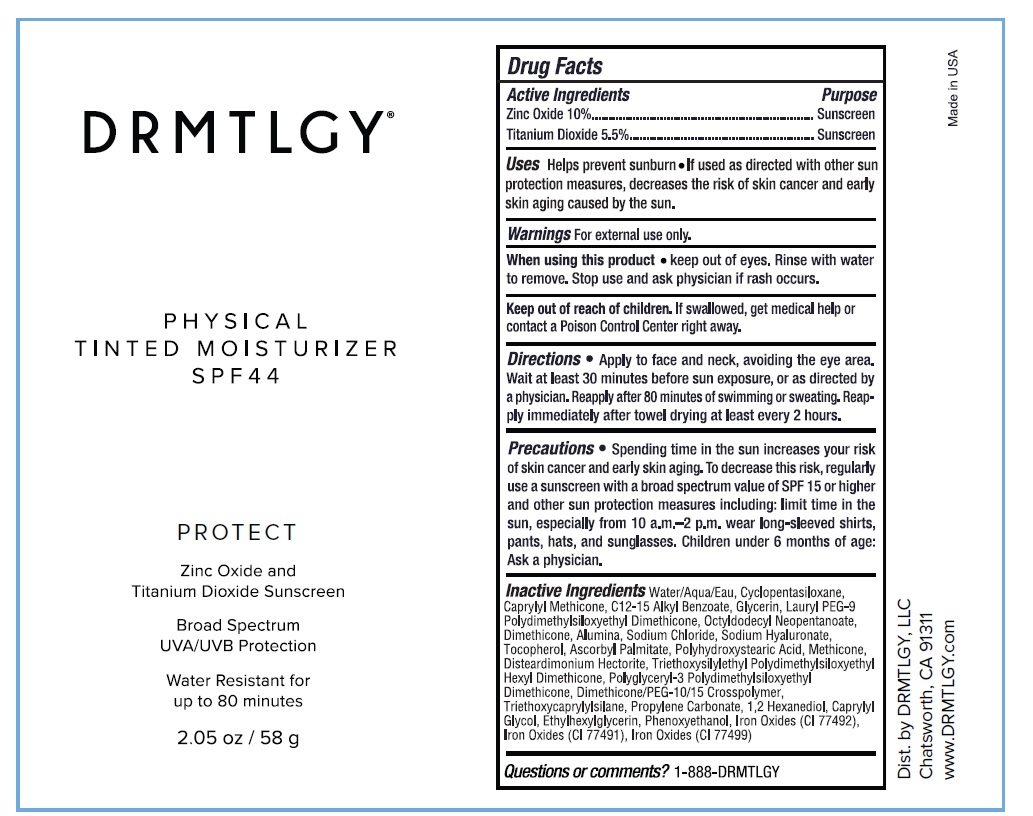 DRUG LABEL: PHYSICAL TINTED MOISTURIZER SPF44
NDC: 83286-010 | Form: CREAM
Manufacturer: Drmtlgy, LLC
Category: otc | Type: HUMAN OTC DRUG LABEL
Date: 20251106

ACTIVE INGREDIENTS: ZINC OXIDE 10 g/100 g; TITANIUM DIOXIDE 5.5 g/100 g
INACTIVE INGREDIENTS: WATER; CYCLOMETHICONE 5; CAPRYLYL TRISILOXANE; ALKYL (C12-15) BENZOATE; GLYCERIN; LAURYL PEG-9 POLYDIMETHYLSILOXYETHYL DIMETHICONE; OCTYLDODECYL NEOPENTANOATE; DIMETHICONE, UNSPECIFIED; ALUMINUM OXIDE; SODIUM CHLORIDE; HYALURONATE SODIUM; TOCOPHEROL; ASCORBYL PALMITATE; POLYHYDROXYSTEARIC ACID (2300 MW); METHICONE (20 CST); DISTEARDIMONIUM HECTORITE; TRIETHOXYSILYLETHYL POLYDIMETHYLSILOXYETHYL HEXYL DIMETHICONE; POLYGLYCERYL-3 POLYDIMETHYLSILOXYETHYL DIMETHICONE (4000 MPA.S); DIMETHICONE/PEG-10/15 CROSSPOLYMER; TRIETHOXYCAPRYLYLSILANE; PROPYLENE CARBONATE; 1,2-HEXANEDIOL; CAPRYLYL GLYCOL; ETHYLHEXYLGLYCERIN; PHENOXYETHANOL; FERRIC OXIDE YELLOW; FERRIC OXIDE RED; FERROSOFERRIC OXIDE

DRMTLGY® PHYSICAL TINTED MOISTURIZER SPF44

Active Ingredients

Zinc Oxide 10%

Titanium Dioxide 5.5%

Purpose

Sunscreen

Uses

Helps prevent sunburn • If used as directed with other sun protection measures, decreases the risk of skin cancer and early skin aging caused by the sun.

Warnings

For external use only.

When using this product • keep out of eyes. Rinse with water to remove. Stop use and ask physician if rash occurs.

Keep out of reach of children. If swallowed, get medical help or contact a Poison Control Center right away.

Directions

• Apply to face and neck, avoiding the eye area. Wait at least 30 minutes before sun exposure, or as directed by a physician. Reapply after 80 minutes of swimming or sweating. Reapply immediately after towel drying at least every 2 hours.

Precautions

• Spending time in the sun increases your risk of skin cancer and early skin aging. To decrease this risk, regularly use a sunscreen with a broad spectrum value of SPF 15 or higher and other sun protection measures including: limit time in the sun, especially from 10 a.m.-2 p.m. wear long-sleeved shirts, pants, hats, and sunglasses. Children under 6 months of age: Ask a physician.

Inactive Ingredients

Water/Aqua/Eau, Cyclopentasiloxane, Caprylyl Methicone, C12-15 Alkyl Benzoate, Glycerin, Lauryl PEG-9 Polydimethylsiloxyethyl Dimethicone, Octyldodecyl Neopentanoate, Dimethicone, Alumina, Sodium Chloride, Sodium Hyaluronate, Tocopherol, Ascorbyl Palmitate, Polyhydroxystearic Acid, Methicone, Disteardimonium Hectorite, Triethoxysilylethyl Polydimethylsiloxyethyl Hexyl Dimethicone, Polyglyceryl-3 Polydimethylsiloxyethyl Dimethicone, Dimethicone/PEG-10/15 Crosspolymer, Triethoxycaprylylsilane, Propylene Carbonate, 1,2 Hexanediol, Caprylyl Glycol, Ethylhexylglycerin, Phenoxyethanol, Iron Oxides (CI 77492), Iron Oxides (CI 77491), Iron Oxides (CI 77499)

Questions or comments?

1-888-DRMTLGY

PROTECT

Broad Spectrum
UVA/UVB Protection

Water Resistant for up to 80 minutes

Dist. by DRMTLGY, LLC
Chatsworth, CA 91311
www.DRMTLGY.com

Made in USA